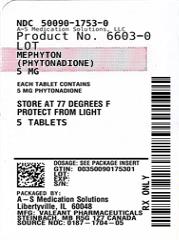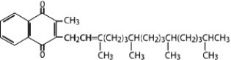 DRUG LABEL: Mephyton
NDC: 50090-1753 | Form: TABLET
Manufacturer: A-S Medication Solutions
Category: prescription | Type: HUMAN PRESCRIPTION DRUG LABEL
Date: 20201117

ACTIVE INGREDIENTS: PHYTONADIONE 5 mg/1 1
INACTIVE INGREDIENTS: Acacia; Silicon Dioxide; Magnesium stearate; Starch, Corn; Talc; CALCIUM PHOSPHATE, UNSPECIFIED FORM; LACTOSE, UNSPECIFIED FORM

Mephyton®
(phytonadione)
Vitamin K1 Tablets

DESCRIPTION

Phytonadione is a vitamin which is a clear, yellow to amber, viscous, and nearly odorless liquid. It is insoluble in water, soluble in chloroform and slightly soluble in ethanol. It has a molecular weight of 450.7.

Phytonadione is 2-methyl-3-phytyl-1, 4-naphthoquinone. Its empirical formula is C31H46O2 and its structural formula is:

Mephyton® (phytonadione) tablets containing 5 mg of phytonadione are yellow, compressed tablets, scored on one side. Inactive ingredients are acacia, calcium phosphate, colloidal silicon dioxide, lactose, magnesium stearate, starch, and talc.

CLINICAL PHARMACOLOGY

Mephyton tablets possess the same type and degree of activity as does naturally-occurring vitamin K, which is necessary for the production via the liver of active prothrombin (factor II), proconvertin (factor VII), plasma thromboplastin component (factor IX), and Stuart factor (factor X). The prothrombin test is sensitive to the levels of three of these four factors – II, VII, and X. Vitamin K is an essential cofactor for a microsomal enzyme that catalyzes the posttranslational carboxylation of multiple, specific, peptide-bound glutamic acid residues in inactive hepatic precursors of factors II, VII, IX, and X. The resulting gamma-carboxyglutamic acid residues convert the precursors into active coagulation factors that are subsequently secreted by liver cells into the blood.

Oral phytonadione is adequately absorbed from the gastrointestinal tract only if bile salts are present. After absorption, phytonadione is initially concentrated in the liver, but the concentration declines rapidly. Very little vitamin K accumulates in tissues. Little is known about the metabolic fate of vitamin K. Almost no free unmetabolized vitamin K appears in bile or urine.

In normal animals and humans, phytonadione is virtually devoid of pharmacodynamic activity. However, in animals and humans deficient in vitamin K, the pharmacological action of vitamin K is related to its normal physiological function, that is, to promote the hepatic biosynthesis of vitamin K-dependent clotting factors.

Mephyton tablets generally exert their effect within 6 to 10 hours.

INDICATIONS AND USAGE

Mephyton is indicated in the following coagulation disorders which are due to faulty formation of factors II, VII, IX and X when caused by vitamin K deficiency or interference with vitamin K activity.

Mephyton tablets are indicated in:

- anticoagulant-induced prothrombin deficiency caused by coumarin or indanedione derivatives;
- hypoprothrombinemia secondary to antibacterial therapy;
- hypoprothrombinemia secondary to administration of salicylates;
- hypoprothrombinemia secondary to obstructive jaundice or biliary fistulas but only if bile salts are administered concurrently, since otherwise the oral vitamin K will not be absorbed.

CONTRAINDICATIONS

Hypersensitivity to any component of this medication.

WARNINGS

An immediate coagulant effect should not be expected after administration of phytonadione.

Phytonadione will not counteract the anticoagulant action of heparin.

When vitamin K1 is used to correct excessive anticoagulant-induced hypoprothrombinemia, anticoagulant therapy still being indicated, the patient is again faced with the clotting hazards existing prior to starting the anticoagulant therapy.

Phytonadione is not a clotting agent, but overzealous therapy with vitamin K1 may restore conditions which originally permitted thromboembolic phenomena. Dosage should be kept as low as possible, and prothrombin time should be checked regularly as clinical conditions indicate.

Repeated large doses of vitamin K are not warranted in liver disease if the response to initial use of the vitamin is unsatisfactory. Failure to respond to vitamin K may indicate a congenital coagulation defect or that the condition being treated is unresponsive to vitamin K.

PRECAUTIONS

General

Vitamin K1 is fairly rapidly degraded by light; therefore, always protect Mephyton from light. Store Mephyton in closed original carton until contents have been used (see HOW SUPPLIED, Storage).

Drug Interactions

Temporary resistance to prothrombin-depressing anticoagulants may result, especially when larger doses of phytonadione are used. If relatively large doses have been employed, it may be necessary when reinstituting anticoagulant therapy to use somewhat larger doses of the prothrombin-depressing anticoagulant or to use one which acts on a different principle, such as heparin sodium.

Laboratory Tests

Prothrombin time should be checked regularly as clinical conditions indicate.

Carcinogenesis, Mutagenesis, Impairment of Fertility

Studies of carcinogenicity or impairment of fertility have not been performed with Mephyton. Mephyton at concentrations up to 2,000 mcg/plate, with or without metabolic activation, was negative in the Ames microbial mutagen test.

Pregnancy

Animal reproduction studies have not been conducted with Mephyton. It is also not known whether Mephyton can cause fetal harm when administered to a pregnant woman or can affect reproduction capacity. Mephyton should be given to a pregnant woman only if clearly needed.

Pediatric Use

Safety and effectiveness in pediatric patients have not been established with Mephyton. Hemolysis, jaundice, and hyperbilirubinemia in newborns, particularly in premature infants, have been reported with vitamin K.

Nursing Mothers

It is not known whether this drug is excreted in human milk. Because many drugs are excreted in human milk, caution should be exercised when Mephyton is administered to a nursing woman.

Geriatric Use

Clinical studies of Mephyton did not include sufficient numbers of subjects aged 65 and over to determine whether they respond differently from younger subjects. Other reported clinical experience has not identified differences in responses between the elderly and younger patients. In general, dose selection for an elderly patient should be cautious, usually starting at the low end of the dosing range, reflecting the greater frequency of decreased hepatic, renal, or cardiac function, and of concomitant disease or other drug therapy.

ADVERSE REACTIONS

Severe hypersensitivity reactions, including anaphylactoid reactions and deaths, have been reported following parenteral administration. The majority of these reported events occurred following intravenous administration.

Transient “flushing sensations” and “peculiar” sensations of taste have been observed with parenteral phytonadione, as well as rare instances of dizziness, rapid and weak pulse, profuse sweating, brief hypotension, dyspnea, and cyanosis.

Hyperbilirubinemia has been observed in the newborn following administration of parenteral phytonadione. This has occurred rarely and primarily with doses above those recommended.

To report SUSPECTED ADVERSE REACTIONS, contact Bausch Health US, LLC at 1-800-321-4576 or FDA at 1-800-FDA-1088 or www.fda.gov/medwatch.

OVERDOSAGE

The intravenous and oral LD50s in the mouse are approximately 1.17 g/kg and greater than 24.18 g/kg, respectively.

DOSAGE AND ADMINISTRATION

Mephyton Tablets Summary of Dosage Guidelines (See package insert for details.)
Adults | Initial Dosage
Anticoagulant-Induced Prothrombin Deficiency (caused by coumarin or indanedione derivatives) | 2.5 mg to 10 mg or up to 25 mg (rarely 50 mg)
Hypoprothrombinemia Due to Other Causes (antibiotics; salicylates or other drugs; factors limiting absorption or synthesis) | 2.5 mg to 25 mg or more (rarely up to 50 mg)

Anticoagulant-Induced Prothrombin Deficiency in Adults

To correct excessively prolonged prothrombin times caused by oral anticoagulant therapy, 2.5 to 10 mg or up to 25 mg initially is recommended. In rare instances 50 mg may be required. Frequency and amount of subsequent doses should be determined by prothrombin time response or clinical condition (see WARNINGS). If, in 12 to 48 hours after oral administration, the prothrombin time has not been shortened satisfactorily, the dose should be repeated.

Hypoprothrombinemia Due to Other Causes in Adults

If possible, discontinuation or reduction of the dosage of drugs interfering with coagulation mechanisms (such as salicylates, antibiotics) is suggested as an alternative to administering concurrent Mephyton. The severity of the coagulation disorder should determine whether the immediate administration of Mephyton is required in addition to discontinuation or reduction of interfering drugs.

A dosage of 2.5 to 25 mg or more (rarely up to 50 mg) is recommended, the amount and route of administration depending upon the severity of the condition and response obtained.

The oral route should be avoided when the clinical disorder would prevent proper absorption. Bile salts must be given with the tablets when the endogenous supply of bile to the gastrointestinal tract is deficient.

HOW SUPPLIED

Product: 50090-1753

NDC: 50090-1753-0 5 TABLET in a BOTTLE

Distributed by:
Bausch Health US, LLC
Bridgewater, NJ 08807 USA

Manufactured by:
Bausch Health Companies Inc.
Steinbach, MB R5G 1Z7, Canada

Mephyton is a trademark of Bausch Health Companies Inc. or its affiliates.
© 2020 Bausch Health Companies Inc. or its affiliates

9571301
20002981

Rev. 08/2020